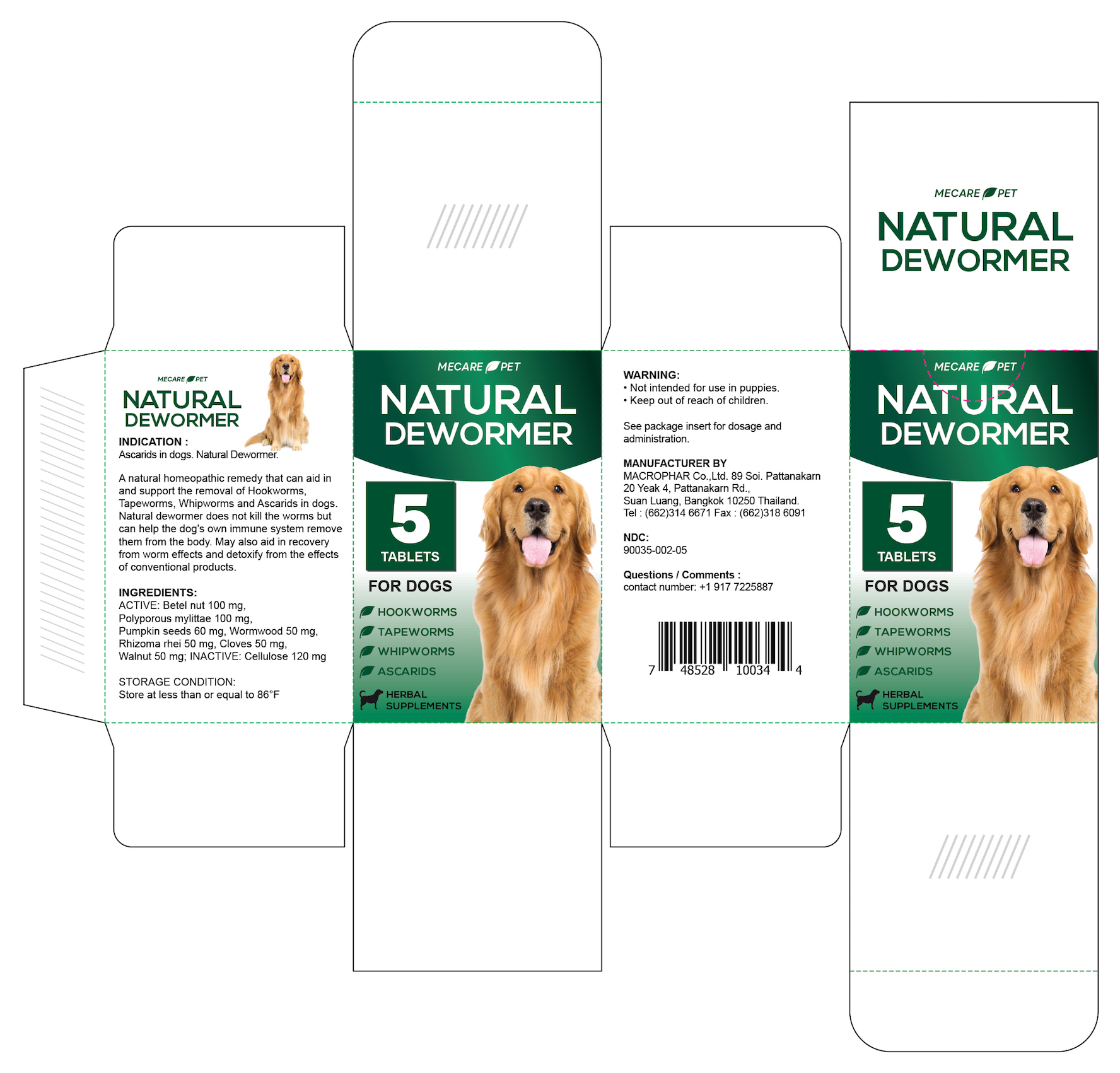 DRUG LABEL: Mecare Pet Natural Dewormer Dogs
NDC: 90035-002 | Form: TABLET
Manufacturer: MacroPhar Co.,Ltd.
Category: homeopathic | Type: OTC ANIMAL DRUG LABEL
Date: 20210212

ACTIVE INGREDIENTS: LACCOCEPHALUM MYLITTAE WHOLE 100 mg/1 1; ARECA CATECHU FRUIT RIND 100 mg/1 1; ENGLISH WALNUT 50 mg/1 1; WORMWOOD 50 mg/1 1; ALISMA PLANTAGO-AQUATICA SUBSP. ORIENTALE ROOT 50 mg/1 1; CLOVE 50 mg/1 1; PUMPKIN SEED 60 mg/1 1
INACTIVE INGREDIENTS: POWDERED CELLULOSE 120 mg/1 1

Mecare Pet Natural Dewormer Dogs

Indications

For the treatment of gastrointestinal tapeworm and roundworm in dogs.

Natural Dewormer is a natural homeopathic remedy that can aid in and support the removal of hookworms, tapeworms, whipworms, and ascarids in dogs. Natural Dewormer does not kill the worms but can help the dog's own immune system remove them from the body. May also aid in recovery from worm effects and detoxify from the effects of conventional products.

Active Ingredients

Betel nut 100 mg, Polyporous mylittae 100 mg, Pumpkin seeds 60 mg, Wormwood 50 mg, Rhizoma rhei 50 mg, Cloves 50 mg, Walnut 50 mg

Inactive Ingredients

Cellulose 120 mg

Storage Condition

Store at less than or equal to 30°C (86°F)

Warning

Not intended for use in puppies.

KEEP OUT OF REACH OF CHILDREN.

Dosage and Administration

PLEASE SEE PACKAGE INSERT FOR COMPLETE DIRECTIONS FOR USE.

OTHER SAFETY INFORMATION

MANUFACTURER BY

MACROPHAR Co.,Ltd. 89 Soi. Pattanakarn
20 Yeak 4, Pattanakarn Rd.,

Suan Luang, Bangkok 10250 Thailand.
Tel : (662)314 6671 Fax : (662)318 6091

NDC:

90035-002-05

Questions and Comments

Contact number: +1 917 7225887

Package Insert

When using this product:

- Any part of unused tablets should be discarded.
- Not for use in dogs weighing less than 6.6 lbs (3 kg)
- Consult a veterinarian before treating pregnant animals for worms.
- Do not exceed the recommended dosage when treating pregnant bitches.
- Wash hands after use.

Dosage and Administration

The tablets can be given directly to the dog or disguised in food. No starvation is needed before or after treatment. For routine worm control, adult dogs should be treated every 3 months.

Dosage

Shown below are dosage recommendations based on the dog's bodyweight:

6.6 - 11 lbs: 1/2 tablets

11 - 22 lbs: 1 tablet

22 - 33 lbs: 1 1/2 tablets

33 - 44 lbs: 2 tablets

44 - 55 lbs: 2 1/2 tablets

55 - 66 lbs: 3 tablets

66 - 77 lbs: 3 1/2 tablets

77 - 88 lbs: 4 tablets

Principal Display Panel

Mecare Pet Natural Dog Dewormer NDC:90035-002-05